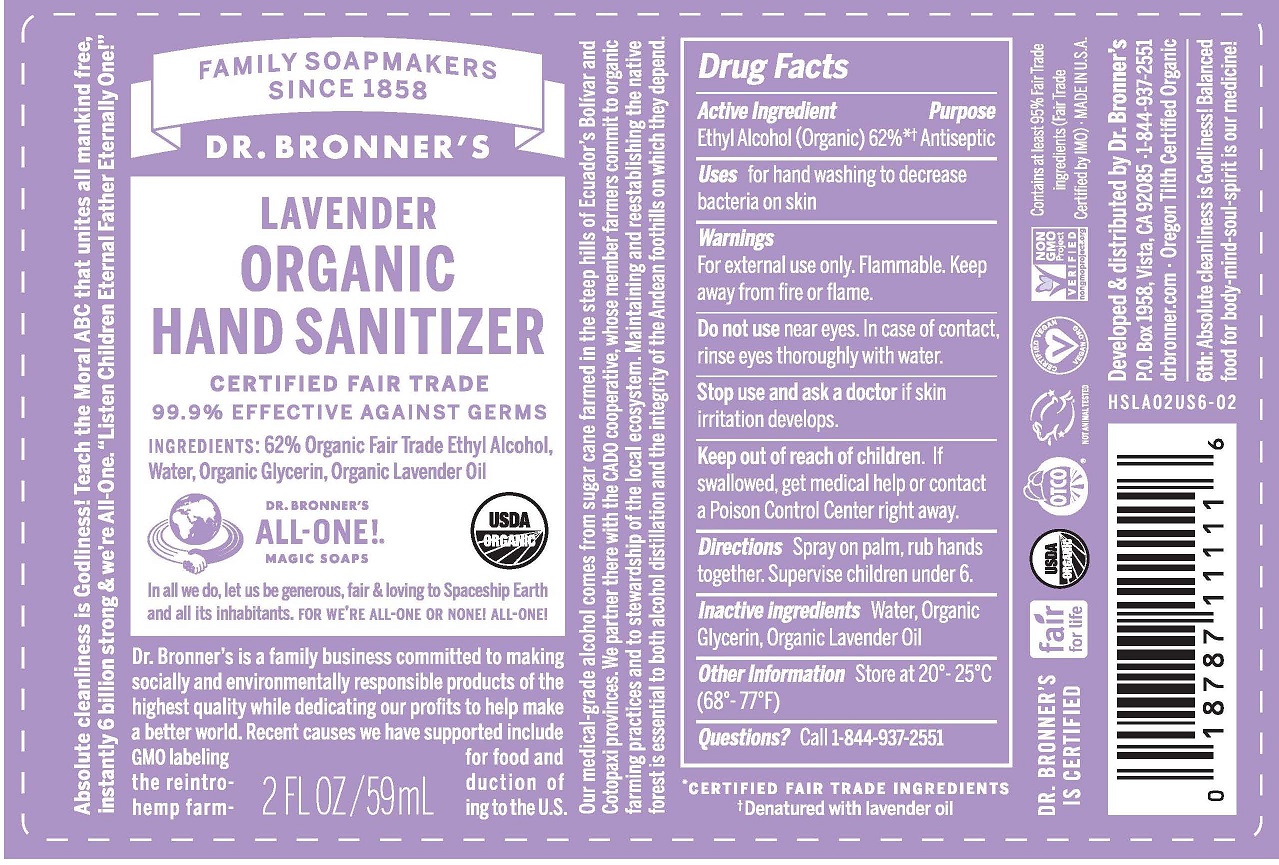 DRUG LABEL: HAND SANITIZING
NDC: 55814-101 | Form: SPRAY
Manufacturer: DR. BRONNER'S MAGIC SOAPS
Category: otc | Type: HUMAN OTC DRUG LABEL
Date: 20251028

ACTIVE INGREDIENTS: ALCOHOL 62 mL/100 mL
INACTIVE INGREDIENTS: WATER; LAVENDER OIL; GLYCERIN

DR BRONNER'S LAVENDER ORGANIC HAND SANITIZER (55814-101)

ACTIVE INGREDIENTS:

ETHYL ALCOHOL (ORGANIC) 62%

PURPOSE:

ANTISEPTIC

USES:

FOR HAND WASHING TO DECREASE BACTERIA ON SKIN.

WARNINGS:

FOR EXTERNAL USE ONLY. FLAMMABLE, KEEP AWAY FROM FIRE OR FLAME.

INACTIVE INGREDIENTS

WATER, ORGANIC GLYCERIN, ORGANIC LAVENDER OIL

KEEP OUT OF REACH OF CHILDREN. IF SWALLOWED, GET MEDICAL HELP OR CONTACT A POISON CONTROL CENTER RIGHT AWAY.

DO NOT USE NEAR EYES. IN CASE OF CONTACT, RINSE EYES THOROUGHLY WITH WATER.

STOP USE AND ASK A DOCTOR IF SKIN IRRITATION DEVELOPS.

DIRECTIONS

SPRAY ON PALM, RUB HANDS TOGETHER. SUPERVISE CHILDREN UNDER 6.

OTHER INFORMATION

STORE AT 20° - 25°C (68° - 77°F)

QUESTIONS?

CALL 760-743-2211